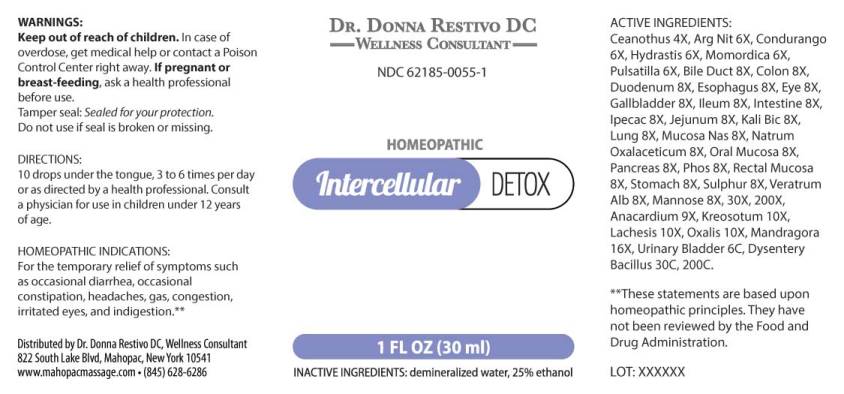 DRUG LABEL: Intercellular Detox
NDC: 62185-0055 | Form: LIQUID
Manufacturer: Dr. Donna Restivo DC
Category: homeopathic | Type: HUMAN OTC DRUG LABEL
Date: 20240118

ACTIVE INGREDIENTS: CEANOTHUS AMERICANUS LEAF 4 [hp_X]/1 mL; SILVER NITRATE 6 [hp_X]/1 mL; MARSDENIA CONDURANGO BARK 6 [hp_X]/1 mL; GOLDENSEAL 6 [hp_X]/1 mL; MOMORDICA BALSAMINA IMMATURE FRUIT 6 [hp_X]/1 mL; PULSATILLA PRATENSIS WHOLE 6 [hp_X]/1 mL; SUS SCROFA BILE DUCT 8 [hp_X]/1 mL; SUS SCROFA COLON 8 [hp_X]/1 mL; SUS SCROFA DUODENUM 8 [hp_X]/1 mL; SUS SCROFA ESOPHAGUS 8 [hp_X]/1 mL; SUS SCROFA EYE 8 [hp_X]/1 mL; SUS SCROFA GALLBLADDER 8 [hp_X]/1 mL; SUS SCROFA ILEUM 8 [hp_X]/1 mL; PORK INTESTINE 8 [hp_X]/1 mL; IPECAC 8 [hp_X]/1 mL; SUS SCROFA JEJUNUM 8 [hp_X]/1 mL; POTASSIUM DICHROMATE 8 [hp_X]/1 mL; SUS SCROFA LUNG 8 [hp_X]/1 mL; SUS SCROFA NASAL MUCOSA 8 [hp_X]/1 mL; SODIUM DIETHYL OXALACETATE 8 [hp_X]/1 mL; SUS SCROFA ORAL MUCOSA 8 [hp_X]/1 mL; SUS SCROFA PANCREAS 8 [hp_X]/1 mL; PHOSPHORUS 8 [hp_X]/1 mL; SUS SCROFA RECTAL MUCOSA 8 [hp_X]/1 mL; SUS SCROFA STOMACH 8 [hp_X]/1 mL; SULFUR 8 [hp_X]/1 mL; VERATRUM ALBUM ROOT 8 [hp_X]/1 mL; MANNOSE, D- 8 [hp_X]/1 mL; SEMECARPUS ANACARDIUM JUICE 9 [hp_X]/1 mL; WOOD CREOSOTE 10 [hp_X]/1 mL; LACHESIS MUTA VENOM 10 [hp_X]/1 mL; OXALIS ACETOSELLA LEAF 10 [hp_X]/1 mL; MANDRAGORA OFFICINARUM ROOT 16 [hp_X]/1 mL; SUS SCROFA URINARY BLADDER 6 [hp_C]/1 mL; SHIGELLA DYSENTERIAE 30 [hp_C]/1 mL
INACTIVE INGREDIENTS: WATER; ALCOHOL

DRUG FACTS:

ACTIVE INGREDIENTS:

Ceanothus Americanus 4X, Argentum Nitricum 6X, Condurango 6X, Hydrastis Canadensis 6X, Momordica Balsamina 6X, Pulsatilla (Pratensis) 6X, Bile Duct (Suis) 8X, Colon (Suis) 8X, Duodenum (Suis) 8X, Esophagus (Suis) 8X, Eye (Suis) 8X, Gallbladder (Suis) 8X, Ileum (Suis) 8X, Intestine (Suis) 8X, Ipecacuanha 8X, Jejunum (Suis) 8X, Kali Bichromicum 8X, Lung (Suis) 8X, Mucosa Nasalis Suis 8X, Natrum Oxalaceticum 8X, Oral Mucosa (Suis) 8X, Pancreas Suis 8X, Phosphorus 8X, Rectal Mucosa (Suis) 8X, Stomach (Suis) 8X, Sulphur 8X, Veratrum Album 8X, Mannose 8X, 30X, 200X, Anacardium Orientale 9X, Kreosotum 10X, Lachesis Mutus 10X, Oxalis Acetosella 10X, Mandragora Officinarum 16X, Urinary Bladder (Suis) 6C, Dysentery Bacillus 30C, 200C.

HOMEOPATHIC INDICATIONS:

For the temporary relief of symptoms such as occasional diarrhea, occasional constipation, headaches, gas, congestion, irritated eyes, and indigestion.**

**These statements are based upon homeopathic principles. They have not been reviewed by the Food and Drug Administration.

WARNINGS:

Keep out of reach of children. In case of overdose, get medical help or contact or a Poison Control Center right away.

If pregnant or breast-feeding, ask a health professional before use.

Tamper seal: "Sealed for Your Protection." Do not use if seal is broken or missing.

Keep out of reach of children. In case of overdose, get medical help or contact or a Poison Control Center right away.

DIRECTIONS:

10 drops under the tongue, 3 to 6 times per day or as directed by a health professional. Consult a physician for use in children under 12 years of age.

HOMEOPATHIC INDICATIONS:

For the temporary relief of symptoms such as occasional diarrhea, occasional constipation, headaches, gas, congestion, irritated eyes, and indigestion.**

**These statements are based upon homeopathic principles. They have not been reviewed by the Food and Drug Administration.

INACTIVE INGREDIENTS:

demineralized water, 25% ethanol

QUESTIONS:

Distributed by Dr. Donna Restivo DC, Wellness Consultant

822 South Lake Blvd, Mahopac, New York 10541

www.mahopacmassage.com • (845) 628-6286

PACKAGE LABEL DISPLAY:

DR. DONNA RESTIVO DC
WELLNESS CONSULTANT
NDC 62185-0055-1
HOMEOPATHIC
Intercellular DETOX
1 FL OZ (30 ml)